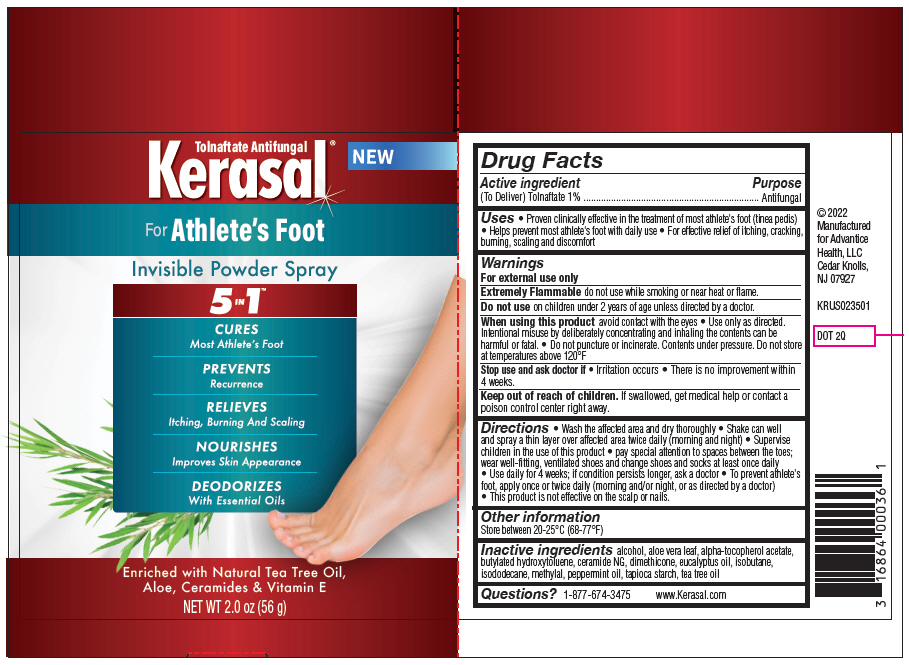 DRUG LABEL: Kerasal Athletes Foot powder
NDC: 16864-110 | Form: SPRAY
Manufacturer: Advantice Health, LLC
Category: otc | Type: HUMAN OTC DRUG LABEL
Date: 20260113

ACTIVE INGREDIENTS: TOLNAFTATE 1 g/100 g
INACTIVE INGREDIENTS: .ALPHA.-TOCOPHEROL ACETATE; ALOE VERA LEAF; BUTYLATED HYDROXYTOLUENE; CERAMIDE NG; DIMETHICONE; EUCALYPTUS OIL; ISOBUTANE; ISODODECANE; PEPPERMINT OIL; STARCH, TAPIOCA; TEA TREE OIL; ALCOHOL

Kerasal®Athlete's Foot Powder Spray

Drug Facts

Active ingredient

(To Deliver) Tolnaftate 1%

Purpose

Antifungal

Uses

- Proven clinically effective in the treatment of most athlete's foot (tinea pedis)
- Helps prevent most athlete's foot with daily use
- For effective relief of itching, cracking, burning, scaling and discomfort

Warnings

For external use only

Extremely Flammabledo not use while smoking or near heat or flame.

DO NOT USE

Do not useon children under 2 years of age unless directed by a doctor.

When using this productavoid contact with the eyes

- Use only as directed. Intentional misuse by deliberately concentrating and inhaling the contents can be harmful or fatal.
- Do not puncture or incinerate. Contents under pressure. Do not store at temperatures above 120°F

Stop use and ask doctor if

- Irritation occurs
- There is no improvement within 4 weeks.

Keep out of reach of children.If swallowed, get medical help or contact a poison control center right away.

Directions

- Wash the affected area and dry thoroughly
- Shake can well and spray a thin layer over affected area twice daily (morning and night)
- Supervise children in the use of this product
- pay special attention to spaces between the toes; wear well-fitting, ventilated shoes and change shoes and socks at least once daily
- Use daily for 4 weeks; if condition persists longer, ask a doctor
- To prevent athlete's foot, apply once or twice daily (morning and/or night, or as directed by a doctor)
- This product is not effective on the scalp or nails.

Other information

Store between 20-25°C (68-77°F)

Inactive ingredients

alcohol, aloe vera leaf, alpha-tocopherol acetate, butylated hydroxytoluene, ceramide NG, dimethicone, eucalyptus oil, isobutane, isododecane, methylal, peppermint oil, tapioca starch, tea tree oil

Questions?

1-877-674-3475
www.Kerasal.com

PRINCIPAL DISPLAY PANEL - 56 g Can Label

Tolnaftate Antifungal
Kerasal®

NEW

For Athlete's Foot

Invisible Powder Spray

5 IN 1™

CURES
Most Athlete's Foot

PREVENTS
Recurrence

RELIEVES
Itching, Burning And Scaling

NOURISHES
Improves Skin Appearance

DEODORIZES
With Essential Oils

Enriched with Natural Tea Tree Oil,
Aloe, Ceramides & Vitamin E

NET WT 2.0 oz (56 g)